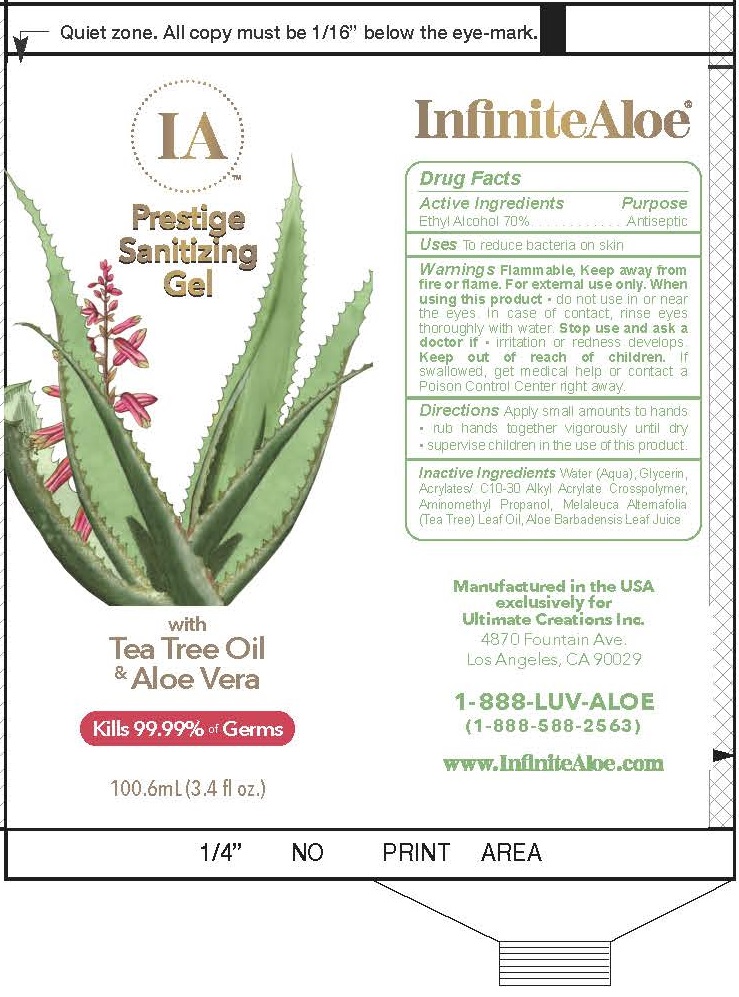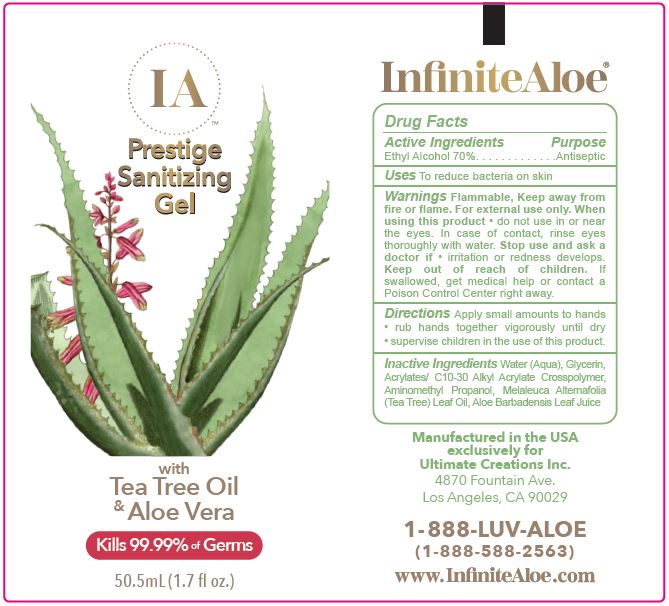 DRUG LABEL: PRESTIGE SANITIZING
NDC: 69069-201 | Form: GEL
Manufacturer: Economical Solutions, Inc. (DBA INFINITE ALOE)
Category: otc | Type: HUMAN OTC DRUG LABEL
Date: 20200703

ACTIVE INGREDIENTS: ALCOHOL 70 mL/100 mL
INACTIVE INGREDIENTS: GLYCERIN; CARBOMER INTERPOLYMER TYPE A (ALLYL SUCROSE CROSSLINKED); AMINOMETHYLPROPANOL; TEA TREE OIL; ALOE VERA LEAF

ACTIVE INGREDIENTS

ETHYL ALCOHOL 70%

PURPOSE

ANTISEPTIC

USES

TO REDUCE BACTERIA ON SKIN

WARNINGS

Flammable, Keep away from fire or flame. For external use only.

When using this product
• do not use in or near the eyes. In case of contact, rinse eyes thoroughly with water.

Stop use and ask a doctor if
• irritation or redness develops.

Keep out of reach of children. If swallowed, get medical help or contact a Poison Control Center right away.

DIRECTIONS

Apply small amounts to hands

- rub hands together vigorously until dry
- supervise children in the use of this product.

INACTIVE INGREDIENTS

Water (Aqua), Glycerin, Acrylates/C10-30 Alkyl Acrylate Crosspolymer, Aminomethyl Propanol, Melaleuca Alternafolia (Tea Tree) Leaf Oil, Aloe Barbadensis Leaf Juice